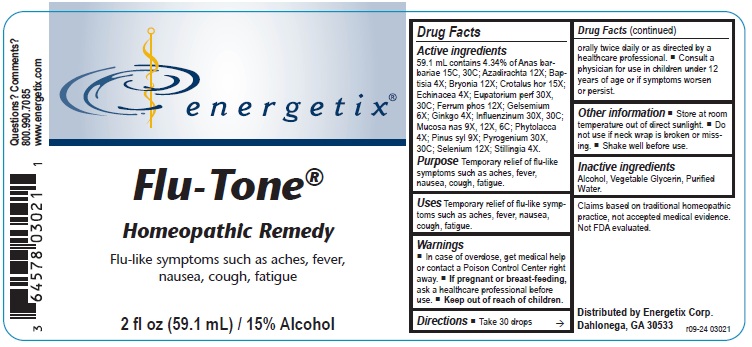 DRUG LABEL: Flu-Tone
NDC: 64578-0136 | Form: LIQUID
Manufacturer: Energetix Corporation
Category: homeopathic | Type: HUMAN OTC DRUG LABEL
Date: 20250715

ACTIVE INGREDIENTS: CAIRINA MOSCHATA HEART/LIVER AUTOLYSATE 15 [hp_C]/1 mL; AZADIRACHTA INDICA BARK 12 [hp_X]/1 mL; BAPTISIA TINCTORIA ROOT 4 [hp_X]/1 mL; BRYONIA ALBA ROOT 12 [hp_X]/1 mL; CROTALUS HORRIDUS HORRIDUS VENOM 15 [hp_X]/1 mL; ECHINACEA ANGUSTIFOLIA 4 [hp_X]/1 mL; EUPATORIUM PERFOLIATUM FLOWERING TOP 30 [hp_X]/1 mL; FERRUM PHOSPHORICUM 12 [hp_X]/1 mL; GELSEMIUM SEMPERVIRENS ROOT 6 [hp_X]/1 mL; GINKGO 4 [hp_X]/1 mL; INFLUENZA A VIRUS A/SINGAPORE/GP1908/2015 IVR-180 (H1N1) ANTIGEN (FORMALDEHYDE INACTIVATED) 30 [hp_X]/1 mL; INFLUENZA A VIRUS A/SINGAPORE/INFIMH-16-0019/2016 NIB-104 (H3N2) ANTIGEN (FORMALDEHYDE INACTIVATED) 30 [hp_X]/1 mL; INFLUENZA B VIRUS B/MARYLAND/15/2016 ANTIGEN (FORMALDEHYDE INACTIVATED) 30 [hp_X]/1 mL; INFLUENZA B VIRUS B/PHUKET/3073/2013 ANTIGEN (FORMALDEHYDE INACTIVATED) 30 [hp_X]/1 mL; SUS SCROFA NASAL MUCOSA 9 [hp_X]/1 mL; PHYTOLACCA AMERICANA ROOT 4 [hp_X]/1 mL; PINUS SYLVESTRIS LEAFY TWIG 9 [hp_X]/1 mL; RANCID BEEF 30 [hp_X]/1 mL; SELENIUM 12 [hp_X]/1 mL; STILLINGIA SYLVATICA ROOT 4 [hp_X]/1 mL
INACTIVE INGREDIENTS: WATER; ALCOHOL; GLYCERIN

Flu-Tone

ACTIVE INGREDIENT

Active ingredients: 59.1 mL contains 4.34% of Anas barbariae 15C, 30C; Azadirachta 12X; Baptisia 4X; Bryonia 12X; Crotalus hor 15X; Echinacea 4X; Eupatorium perf 30X, 30C; Ferrum phos 12X; Gelsemium 6X; Ginkgo 4X; Influenzinum 30X, 30C; Mucosa nas 9X, 12X, 6C; Phytolacca 4X; Pinus syl 9X; Pyrogenium 30X, 30C; Selenium 12X; Stillingia 4X.

Claims based on traditional homeopathic practice, not accepted medical evidence. Not FDA evaluated.

Uses

Temporary relief of flu-like symptoms such as aches, fever, nausea, cough, fatigue.

Warnings

In case of overdose, get medical help or call a Poison Control Center right away.
If pregnant or breast-feeding, ask a health professional before use.

Keep out of reach of children.

DOSAGE AND ADMINISTRATION

Take 30 drops orally twice daily or as directed by a healthcare professional.
Consult a physician for use in children under 12 years of age or if symptoms worsen or persist.

Other information

- Store at room temperature out of direct sunlight.
- Do not use if neck wrap is broken or missing.
- Shake well before use.

Inactive ingredients Alcohol, Vegetable Glycerin, Purified Water.

QUESTIONS

Distributed by Energetix Corp
Dahlonega, GA 30533
Questions? Comments?
800.990.7085

www.energetix.com

PACKAGE LABEL

energetix

Flu-Tone
Homeopathic Remedy

Flu-like symptoms such as aches, fever,

nausea, cough, fatigue.

2 fl oz (59.1 mL) / 15% Alcohol

PURPOSE

Purpose Temporary relief of flu-like symptoms such as aches, fever, nausea, cough, fatigue.